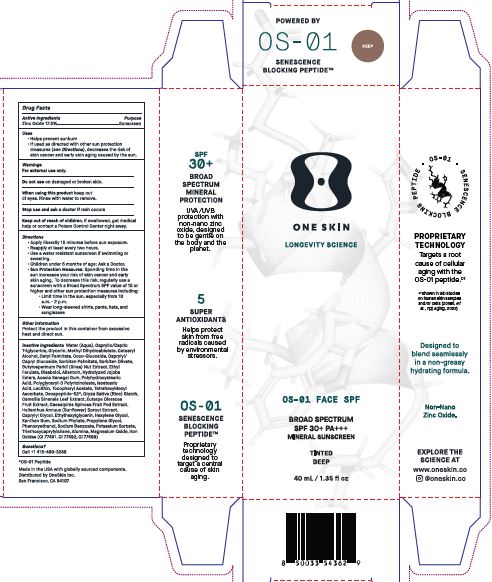 DRUG LABEL: OS-01 FACE SPF BS SPF 30 TINTED DEEP
NDC: 84451-005 | Form: CREAM
Manufacturer: ONESKIN INC.
Category: otc | Type: HUMAN OTC DRUG LABEL
Date: 20250519

ACTIVE INGREDIENTS: ZINC OXIDE 17.5 g/100 g
INACTIVE INGREDIENTS: SORBITAN PALMITATE; SODIUM PHYTATE; BISABOLOL; CETYL PALMITATE; COCO GLUCOSIDE; CAMELLIA SINENSIS LEAF; XANTHAN GUM; CETEARYL ALCOHOL; METHYL DIHYDROABIETATE; CAPRYLYL/CAPRYL GLUCOSIDE; ACACIA SENEGAL GUM; POLYGLYCERYL-3 PENTARICINOLEATE; CI 77499; WATER; CAPRYLYL GLYCOL; MAGNESIUM OXIDE; CI 77491; .ALPHA.-TOCOPHEROL ACETATE; HELIANTHUS ANNUUS SPROUT; TRIETHOXYCAPRYLYLSILANE; HEXYLENE GLYCOL; ETHYL FERULATE; LECITHIN, SUNFLOWER; ORYZA SATIVA (RICE) STARCH; PHENOXYETHANOL; CI 77492; SORBITAN OLIVATE; SHEANUT; CAESALPINIA SPINOSA FRUIT POD; ETHYLHEXYLGLYCERIN; CAPRYLIC/CAPRIC TRIGLYCERIDE; GLYCERIN; ALLANTOIN; HYDROLYZED JOJOBA ESTERS; POLYHYDROXYSTEARIC ACID (2300 MW); ISOSTEARIC ACID; PROPYLENE GLYCOL; SODIUM BENZOATE; POTASSIUM SORBATE; TETRAHEXYLDECYL ASCORBATE; ACAI; ALUMINA

Drug Facts

Active ingredients : Zinc Oxide 17.5%.

Purpose : Sunscreen

Uses

Helps prevent sunburn.

If used as directed with other sun protection measures (see Directions), decreases the risk of skin cancer and early skin aging caused by the sun.

Warnings

For external use only.

Do not use on damaged or broken skin.

When using this product keep out of eyes.

Rinse with water to remove.

Stop use and ask a doctor if rash occurs.

Keep out of reach of children. If swallowed, get medical help or contact a Poison Control Center right away.

Directions:

Apply liberally 15 minutes before sun exposure.
Reapply at least every 2 hours
Use a water-resistant sunscreen If swimming or sweating.
Children under 6 months of age: Ask a Doctor.
Sun Probation Measures: Spending time in the sun increases your risk of skin cancer and early skin aging.

To decrease this risk, regularly use a sunscreen with a Broad Spectrum SPF value of 15 or higher and other sun protection measures including:

Limit time in the sun. especially from 10 a.m. - 2 p.m.

Wear long-sleeved shirts, pants, hats, and sunglasses

Other information

Protect the product in this container from excessive heat and direct sun.

Inactive Ingredients
Water (Aqua),Caprylic/Capric Triglyceride, Glycerin, Methyl Dihydroabietate, Cetearyl Alcohol, Cetyl Palmitate, Coco-Glucoside, Caprylyl/Capryl Glucoside, Sorbitan Palmitate, Sorbitan Olivate, Butyrospermum Parkii (Shea) Nut Extract, Ethyl Ferulate, Bisabolol, Allantoin, Hydrolyzed Jojoba Esters, Acacia Senegal Gum, Polyhydroxystearic acid, Polyglyceryl-3 Polyricinoleate, Isostearic acid, Lecithin, Tocopheryl Acetate, Tetrahexyldecyl Ascorbate, Decapeptide-52*,Oryza Sativa (Rice) Starch, Camellia Sinensis Leaf Extract, Euterpe Oleracea Fruit Extract, Caesalpinia Spinosa Fruit Pod Extract, Helianthus Annuus (Sunflower) Sprout Extract, Caprylyl Glycol, Ethylhexylglycerin, Hexylene Glycol, Xanthan Gum, Sodium Phytate, Propylene Glycol, Phenoxyethanol, Sodium Benzoate, Potassium Sorbate, Triethoxycaprylylsilane, Alumina, Magnesium Oxide, Iron Oxides (CI 77491, CI 77492, CI 77499)